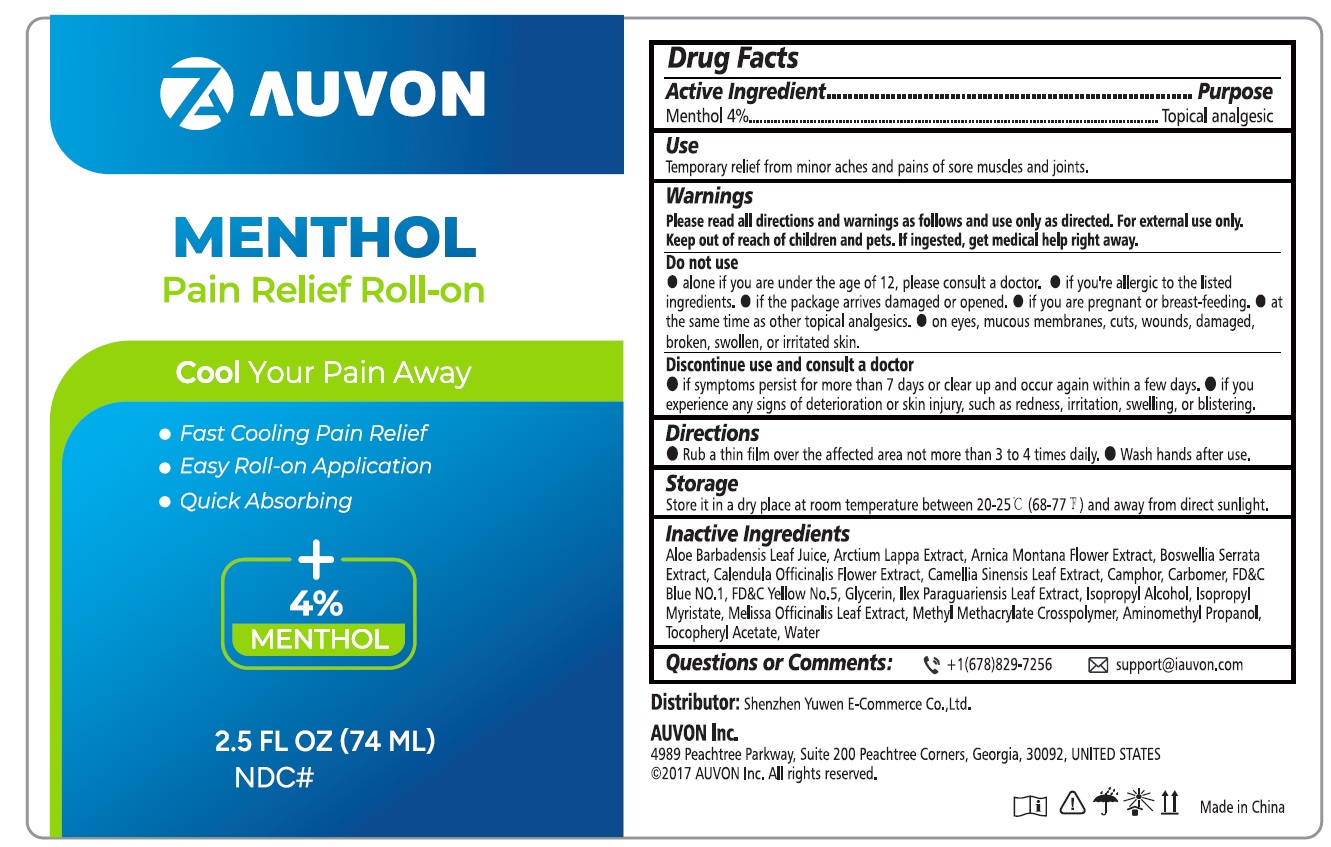 DRUG LABEL: AUVON Pain Relief Roll-on
NDC: 83391-003 | Form: SOLUTION
Manufacturer: SHENZHEN YUWEN E-COMMERCE CO., LTD.
Category: otc | Type: HUMAN OTC DRUG LABEL
Date: 20241208

ACTIVE INGREDIENTS: MENTHOL 4 g/100 mL
INACTIVE INGREDIENTS: WATER; GLYCERIN; ALOE VERA LEAF; ARCTIUM LAPPA WHOLE; ARNICA MONTANA FLOWER; INDIAN FRANKINCENSE; CALENDULA OFFICINALIS FLOWER; GREEN TEA LEAF; CAMPHOR (NATURAL); CARBOMER 940; FD&C BLUE NO. 1; FD&C YELLOW NO. 5; ILEX PARAGUARIENSIS LEAF; ISOPROPYL ALCOHOL; ISOPROPYL MYRISTATE; MELISSA OFFICINALIS LEAF; POLY(METHYL METHACRYLATE; 450000 MW); AMINOMETHYLPROPANOL; .ALPHA.-TOCOPHEROL ACETATE

83391-003 Menthol Pain Relief Roll-on

MENTHOL AUVON Pain Relief Roll-on

Drug Facts

Active ingredients

Menthol 4%

Purposes

Topical Analgestic

Use

Temporary relief from minor aches and pains of sore muscles and joints

Warnings

Please read all directions and warnings as follows and use only as directed. For external use only

Do not use

- If you are under 12 years of age, please consult a doctor
- If you are allergic to the listed ingredients
- If the package arrives damaged or opened.
- If you are pregnent or breast feeding
- At the same time as other topical analgesics
- On eyes, mucous membranes, cuts, wounds, damaged, broken, swollen, or irritated skin

Discontinue use and consult a doctor

- if symptoms persist for more than 7 days or clear up and occur again within a few days
- If you experience any signs of deterioration or skin injury, such as redness, irritation, swelling, or blistering

Keep outof reach of children and pets.

If ingested, get medical help right away.

Directions

- Rub a thin film over the affected area not more than 3 to 4 times daily
- Wash hands after use

Storage

Store it in a dry place at room temperature between 20-25 C (68-77F) and away from direct sunlight.

Inactive ingredients

Aloe Barbadensis Leaf Juice, Arctium Lappa Extract, Arnica Montana Flower Extract, Boswellia Serrata Extract, Calendula Officinalis Flower Extract, Camellia Sinensis Leaf Extract, Camphor, Carbomer, FD&C Blue NO.1, FD&C Yellow No.5, Glycerin, Ilex Paraguariensis Leaf Extract, Isopropyl Alcohol, IsopropyI Myristate, Melissa Officinalis Leaf Extract, Methyl Methacrylate Crosspolymer, Aminomethyl Propanol, Tocopheryl Acetate, Water